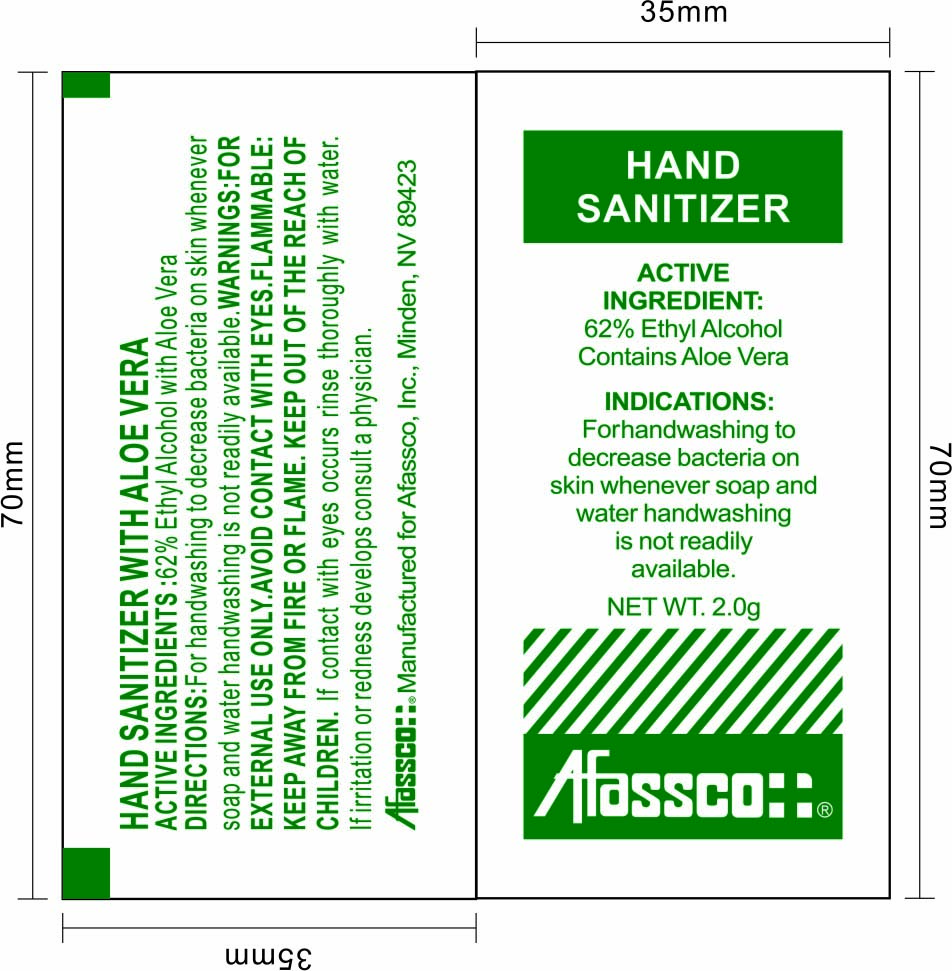 DRUG LABEL: Afassco Hand Sanitizer
NDC: 71734-206 | Form: LIQUID
Manufacturer: JIANGMEN SHUIZIRUN SANITARY ARTICLES CO., LTD.
Category: otc | Type: HUMAN OTC DRUG LABEL
Date: 20181018

ACTIVE INGREDIENTS: ALCOHOL 62 mL/100 mL
INACTIVE INGREDIENTS: ALOE VERA LEAF; GLYCERIN; CARBOMER 934; WATER

Drug Fact

Active Ingredient

Ethyl Alcohol 62%

Purpose

Antiseptic wash hands without water

Uses

for handwashing to decrease bacteria on skin whenever soap and water handwashing is not readily available.

Warnings

For external use only.

Avoid contact with eyes.

Flammable: keep away from fire or flame

Keep out of the reach of children.

If contact with eyes occurs rinse thoroughly with water.

If irritation or redness develops consult a physician.

When using this product

- keep out of eyes.

consult a physician

if irritation or redness develops

Keep out of reach of children.

keep out of the reach of children

Directions

- for handwashing to decrease bacteria on skin whenever soap and water handwashing is not readily available.

Inactive Ingredients

purified water, glycerine, carbomer, aloe essence